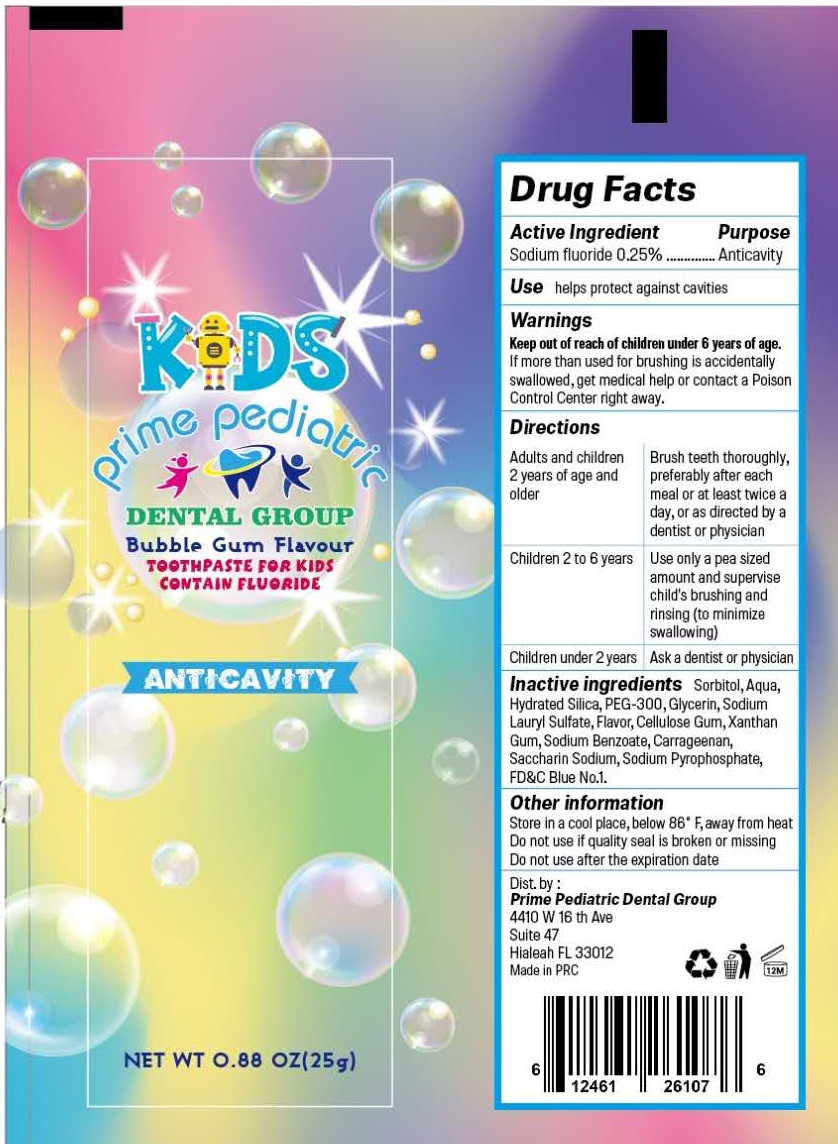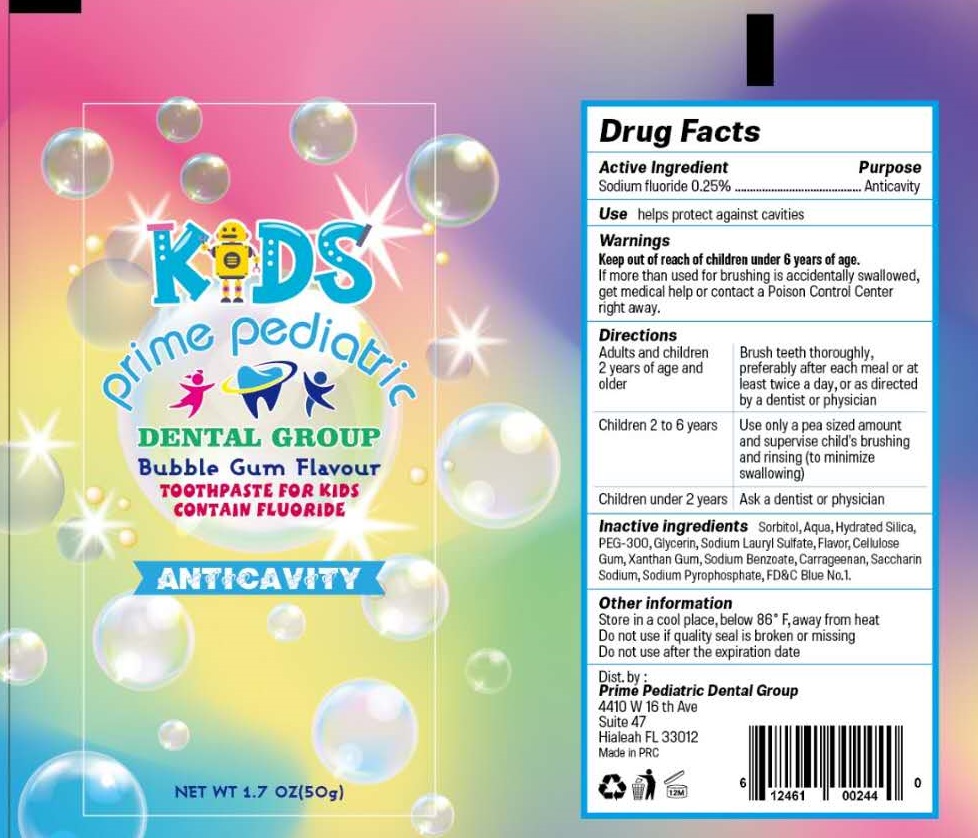 DRUG LABEL: Kids Prime Pediatric Dental Group Anticavity for Kids
NDC: 87053-008 | Form: OINTMENT
Manufacturer: Prime Tooth Care LLC
Category: otc | Type: HUMAN OTC DRUG LABEL
Date: 20260109

ACTIVE INGREDIENTS: SODIUM FLUORIDE 2.5 mg/1 g
INACTIVE INGREDIENTS: SORBITOL; WATER; HYDRATED SILICA; POLYETHYLENE GLYCOL 14000; GLYCERIN; SODIUM LAURYL SULFATE; CARBOXYMETHYLCELLULOSE SODIUM, UNSPECIFIED; XANTHAN GUM; SODIUM BENZOATE; CARRAGEENAN; SACCHARIN SODIUM; SODIUM PYROPHOSPHATE; FD&C BLUE NO. 1

Kids Prime Pediatric Dental Group Anticavity Toothpaste for Kids

Active Ingredient

Sodium fluoride 0.25%

Purpose

Anticavity

Use

helps protect against cavities

Warnings

Keep out of reach of children under 6 years of age.

If more than used for brushing is accidentally swallowed, get medical help or contact a Poison Control Center right away.

Directions

Adults and children 2 years of age and older | Brush teeth thoroughly, preferably after each meal or at least twice a day, or as directed by a dentist or doctor.
Children 2 to 6 years | Use only a pea sized amount and supervise child's brushing and rinsing (to minimize swallowing)
Children under 2 years | Ask a dentist or physician

Inactive ingredients

Sorbitol, Aqua, Hydrated Silica, PEG-300, Glycerin, Sodium Lauryl Sulfate, Flavor, Cellulose Gum, Xanthan Gum, Sodium Benzoate, Carrageenan, Saccharin Sodium, Sodium Pyrophosphate, FD&C Blue No.1.

Other information

Store in a cool place, below 86°F, away from heat
Do not use if quality seal is broken or missing
Do not use after the expiration date